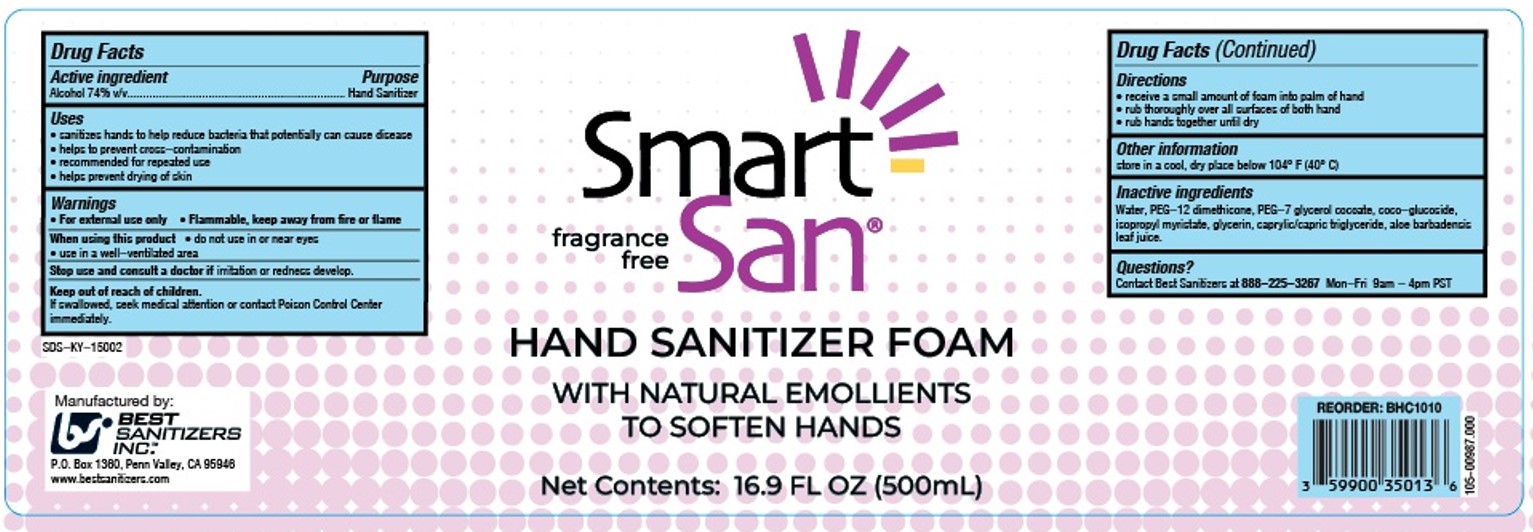 DRUG LABEL: Smart-San Hand Sanitizer Foam
NDC: 59900-352 | Form: LIQUID
Manufacturer: Best Sanitizers, Inc.
Category: otc | Type: HUMAN OTC DRUG LABEL
Date: 20241213

ACTIVE INGREDIENTS: ALCOHOL 74 mL/100 mL
INACTIVE INGREDIENTS: PEG-12 DIMETHICONE (300 CST); PEG-7 GLYCERYL COCOATE; ISOPROPYL MYRISTATE; WATER; COCO-GLUCOSIDE; CAPRYLIC/CAPRIC TRIGLYCERIDE; ALOE BARBADENSIS LEAF JUICE; GLYCERIN

Smart-San Hand Sanitizer Foam 5900-352

Active ingredient

Alcohol 74% v/v

Purpose

Hand Sanitizer

Uses

• sanitizes hands to help reduce bacteria that potentially can cause disease

• helps to prevent cross-contamination

• recommended for repeated use

• helps prevent drying of skin

Warnings

•For external use only • Flammable, keep away from fire or flame

When using this product • do not use in or near eyes

• use in a well-ventilated area

Stop use and consult a doctor if irritation or redness develop.

Keep out of reach of children.

If swallowed, seek medical attention or contact Poison Control Center immediately.

Directions

• receive a small amount of foam into palm of hand

• rub thoroughly over all surfaces of both hands

• rub hands together until dry

Other information

store in a cool, dry place below 104° F (40° C)

Inactive ingredients

Water, PEG-12 dimethicone, PEG-7 glyerol cocoate, coco-glucoside, isopropyl myristate, glycerin, caprylic/capric triglyceride, aloe barbadensis leaf juice.

Questions?

Contact Best Sanitizers at 888-225-3267 Mon-Fri 9am - 4pm PST

PACKAGE LABEL

fragrance

free

Smart-

San

HAND SANITIZER FOAM

WITH NATURAL EMOLLIENTS

TO SOFTEN HANDS

Net Contents: 16.9 FL OZ (500mL)